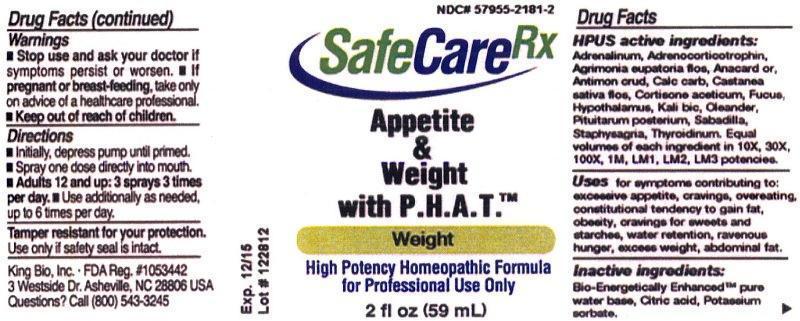 DRUG LABEL: Appetite and Weight with P.H.A.T.
NDC: 57955-2181 | Form: LIQUID
Manufacturer: King Bio Inc.
Category: homeopathic | Type: HUMAN PRESCRIPTION DRUG LABEL
Date: 20130416

ACTIVE INGREDIENTS: EPINEPHRINE 10 [hp_X]/59 mL; CORTICOTROPIN 10 [hp_X]/59 mL; AGRIMONIA EUPATORIA FLOWER 10 [hp_X]/59 mL; SEMECARPUS ANACARDIUM JUICE 10 [hp_X]/59 mL; ANTIMONY TRISULFIDE 10 [hp_X]/59 mL; OYSTER SHELL CALCIUM CARBONATE, CRUDE 10 [hp_X]/59 mL; CASTANEA SATIVA FLOWER 10 [hp_X]/59 mL; CORTISONE ACETATE 10 [hp_X]/59 mL; FUCUS VESICULOSUS 10 [hp_X]/59 mL; BOS TAURUS HYPOTHALAMUS 10 [hp_X]/59 mL; POTASSIUM DICHROMATE 10 [hp_X]/59 mL; NERIUM OLEANDER LEAF 10 [hp_X]/59 mL; SUS SCROFA PITUITARY GLAND 10 [hp_X]/59 mL; SCHOENOCAULON OFFICINALE SEED 10 [hp_X]/59 mL; DELPHINIUM STAPHISAGRIA SEED 10 [hp_X]/59 mL; THYROID, UNSPECIFIED 10 [hp_X]/59 mL
INACTIVE INGREDIENTS: WATER; CITRIC ACID MONOHYDRATE; POTASSIUM SORBATE

Appetite Weight with PHAT

Warnings

- Stop use and ask your doctor if symptoms persist or worsen.
- If pregnant or breast-feeding, take only on advice of a healthcare professional.
- Keep out of reach of children

Tamper resistant for your protection. Use only if safety seal is intact.

Keep out of reach of children.

Dosage and Administration

Directons

- Initially, depress pump until primed.
- Spray one dose directly into mouth.
- Adults 12 and up: 3 sprays 3 times per day.
- Use additionally as needed, up to 6 times per day.

HPUS Active ingredients

Adrenalinum, Adrenocorticotrophin, Agrimonia eupatoria, flos, Anacardium orientale, Antimonium crudum, Calcarea carbonica, Castanea sativa, flos, Cortisone aceticum, Fucus vesiculosus, Hypothalamus, Kali bichromicum, Oleander, Pituitarum posterium, Sabadilla, Staphysagria, Thyroidinum.

Indications and Usage

Uses for symptoms contributing to: excessive appetite, cravings, overeating, constitutional tendency to gain fat, obesity, cravings for sweets and starches, water retention, ravenous hunger, excess weight, abdominal fat.

Inactive Ingredients

Bio-Energetically Enhanced™ pure water base, Citric acid, Potassium sorbate.

Purpose

Uses for symptoms contributing to:

- excessive appetite
- cravings
- overeating
- constitutional tendency to gain fat
- obesity
- cravings for sweets and starches
- water retention
- ravenous hunger
- excess wieght
- abdoninal fat